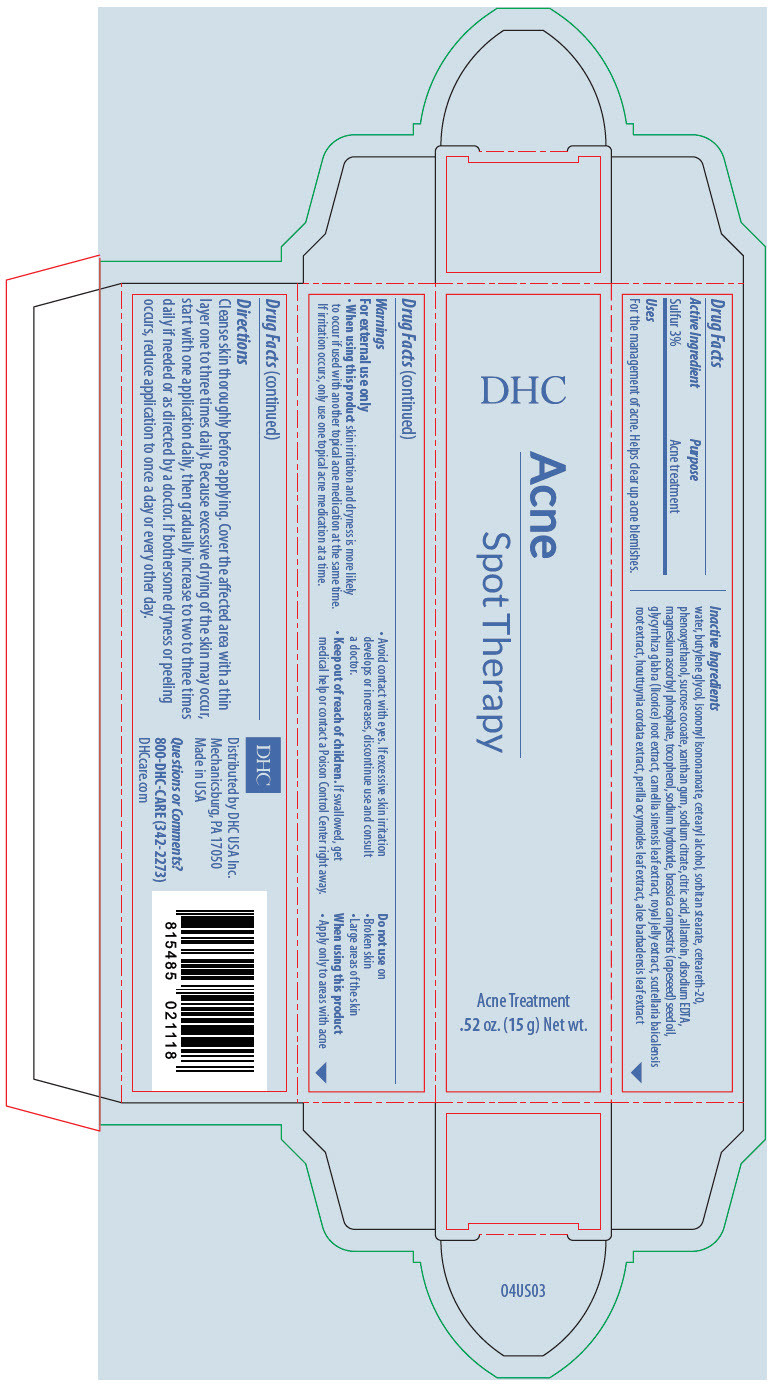 DRUG LABEL: DHC Acne Spot Therapy
NDC: 63433-389 | Form: CREAM
Manufacturer: DHC USA Incorporated
Category: otc | Type: HUMAN OTC DRUG LABEL
Date: 20260124

ACTIVE INGREDIENTS: Sulfur 6 mg/0.2 g
INACTIVE INGREDIENTS: Water; Butylene Glycol; Isononyl Isononanoate; Cetostearyl Alcohol; Sorbitan Monostearate; Sodium Citrate, Unspecified Form; Citric Acid Monohydrate; Phenoxyethanol; Xanthan Gum; Allantoin; .Alpha.-Tocopherol; Brassica Rapa Subsp. Oleifera Oil; Magnesium Ascorbyl Phosphate; Glycyrrhiza Glabra; Royal Jelly; Green Tea Leaf; Houttuynia Cordata Flowering Top; Scutellaria Lateriflora Top; Perilla Frutescens Leaf; Aloe Vera Leaf; Edetate Disodium; Sodium Hydroxide

DHC Acne Spot Therapy

Drug Facts

Active Ingredient

Sulfur 3%

Purpose

Acne treatment

Uses

For the management of acne. Helps clear up acne blemishes.

Warnings

For external use only

- When using this product skin irritation and dryness is more likely to occur if used with another topical acne medication at the same time. If irritation occurs, only use one topical acne medication at a time.
- Avoid contact with eyes. If excessive skin irritation develops or increases, discontinue use and consult a doctor.

- Keep out of reach of children. If swallowed, get medical help or contact a Poison Control Center right away.

Do not use on

- Broken skin
- Large areas of the skin

When using this product

- Apply only to areas with acne

Directions

Cleanse skin thoroughly and tone before applying. Cover the affected area with a thin layer one to three times daily. Because excessive drying of the skin may occur, start with one application daily, then gradually increase to two to three times daily if needed or as directed by a doctor. If bothersome dryness or peeling occurs, reduce application to once a day or every other day.

Inactive Ingredients

water, butylene glycol, isononyl isononanoate, cetearyl alcohol, sorbitan stearate, ceteareth-20, phenoxyethanol, sucrose cocoate, xanthan gum, sodium citrate, citric acid, allantoin, disodium EDTA, magnesium ascorbyl phosphate, tocopherol, sodium hydroxide, brassica campestris (rapeseed) seed oil, glycyrrhiza glabra (licorice) root extract, camellia sinensis leaf extract, royal jelly extract, scutellaria baicalensis root extract, houttuynia cordata extract, perilla ocymoides leaf extract, aloe barbadensis leaf extract

Questions or Comments?

800-DHC-CARE (342-2273)
dhccare.com

Distributed by DHC USA Inc.
Mechanicsburg, PA 17050

PRINCIPAL DISPLAY PANEL - 15 g Tube Box

DHC

Acne
Spot Therapy

Acne Treatment

.52 oz. (15 g) Net wt.